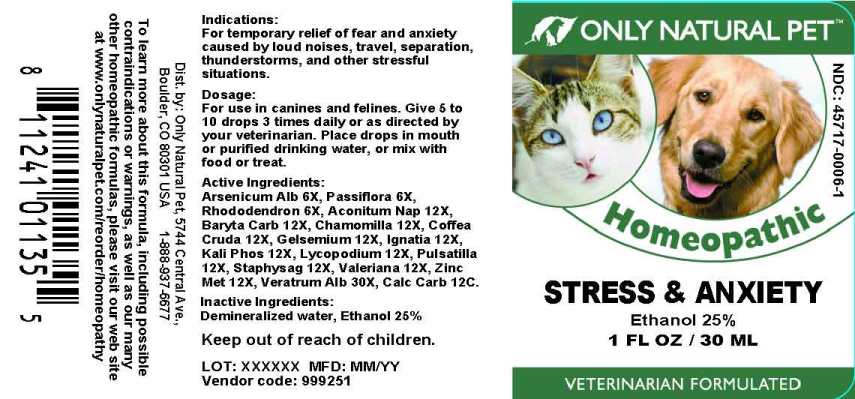 DRUG LABEL: Stress and Anxiety
NDC: 45717-0006 | Form: LIQUID
Manufacturer: Only Natural Pet Store
Category: homeopathic | Type: OTC ANIMAL DRUG LABEL
Date: 20241003

ACTIVE INGREDIENTS: ARSENIC TRIOXIDE 6 [hp_X]/1 mL; PASSIFLORA INCARNATA FLOWERING TOP 6 [hp_X]/1 mL; RHODODENDRON AUREUM LEAF 6 [hp_X]/1 mL; ACONITUM NAPELLUS WHOLE 12 [hp_X]/1 mL; BARIUM CARBONATE 12 [hp_X]/1 mL; MATRICARIA CHAMOMILLA WHOLE 12 [hp_X]/1 mL; ARABICA COFFEE BEAN 12 [hp_X]/1 mL; GELSEMIUM SEMPERVIRENS ROOT 12 [hp_X]/1 mL; STRYCHNOS IGNATII SEED 12 [hp_X]/1 mL; POTASSIUM PHOSPHATE, DIBASIC 12 [hp_X]/1 mL; LYCOPODIUM CLAVATUM SPORE 12 [hp_X]/1 mL; PULSATILLA PRATENSIS WHOLE 12 [hp_X]/1 mL; DELPHINIUM STAPHISAGRIA SEED 12 [hp_X]/1 mL; VALERIAN 12 [hp_X]/1 mL; ZINC 12 [hp_X]/1 mL; VERATRUM ALBUM ROOT 30 [hp_X]/1 mL; OYSTER SHELL CALCIUM CARBONATE, CRUDE 12 [hp_X]/1 mL
INACTIVE INGREDIENTS: WATER; ALCOHOL

Drug Facts:

ACTIVE INGREDIENTS:

Arsenicum Album 6X, Passiflora Incarnata 6X, Rhododendron Chrysanthum 6X, Aconitum Napellus 12X, Baryta Carbonica 12X, Chamomilla 12X, Coffea Cruda 12X, Gelsemium Sempervirens 12X, Ignatia Amara 12X, Kali Phosphoricum 12X, Lycopodium Clavatum 12X, Pulsatilla (Pratensis) 12X, Staphysagria 12X, Valeriana Officinalis 12X, Zincum Metallicum 12X, Veratrum Album 30X, Calcarea Carbonica 12C.

INDICATIONS:

For temporary relief of fear and anxiety caused by loud noises, travel, separation, thunderstorms, and other stressful situations.

WARNINGS:

Keep out of reach of children.

KEEP OUT OF REACH OF CHILDREN:

DIRECTIONS:

For use in canines and felines. Give 5 to 10 drops 3 times daily or as directed by your veterinarian. Place drops in mouth or purified drinking water, or mix with food or treat.

INDICATIONS:

For temporary relief of fear and anxiety caused by loud noises, travel, separation, thunderstorms, and other stressful situations.

INACTIVE INGREDIENTS:

Demineralized water, Ethanol 25%

QUESTIONS:

Dist. by: Only Natural Pet, 5744 Central Ave.,

Boulder, CO 80301 USA 1-888-937-6677

To learn more about this formula, including possible contraindications or warnings, as well as our many other homeopathic formulas, please visit our web site at www.only naturalpet.com/reorder/homeopathy

PACKAGE LABEL DISPLAY

ONLY NATURAL PET

NDC 45717-0006-1

Homeopathic

Stress & Anxiety

1 FL OZ / 30 ML